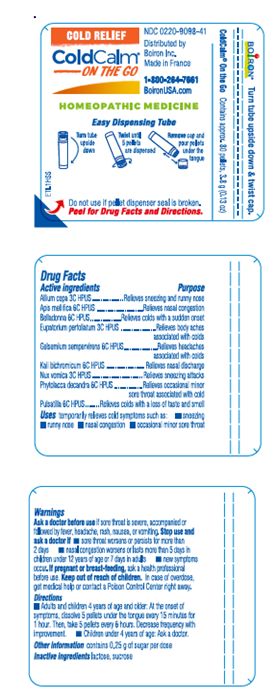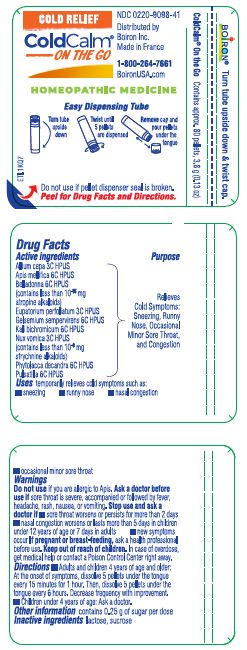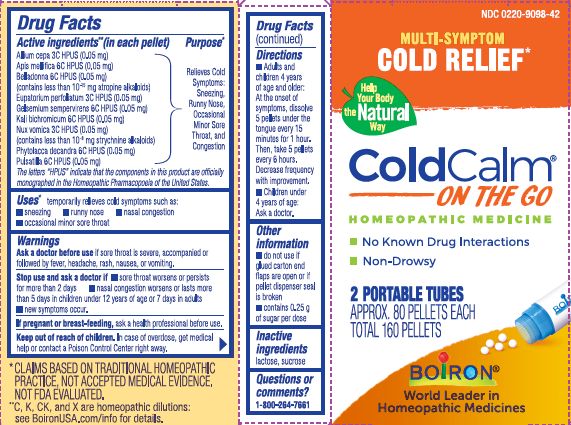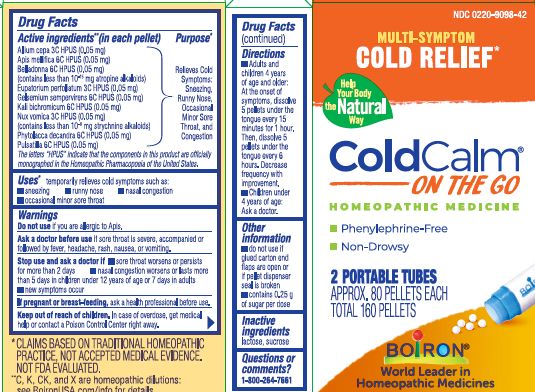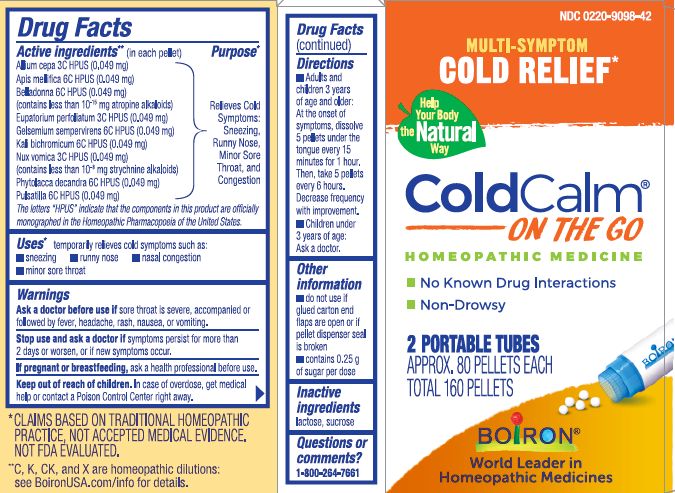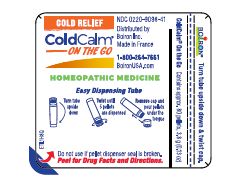 DRUG LABEL: COLDCALM
NDC: 0220-9098 | Form: PELLET
Manufacturer: Boiron
Category: homeopathic | Type: HUMAN OTC DRUG LABEL
Date: 20250415

ACTIVE INGREDIENTS: PHYTOLACCA AMERICANA ROOT 6 [hp_C]/1 1; APIS MELLIFERA 6 [hp_C]/1 1; ATROPA BELLADONNA 6 [hp_C]/1 1; ONION 3 [hp_C]/1 1; PULSATILLA VULGARIS 6 [hp_C]/1 1; POTASSIUM DICHROMATE 6 [hp_C]/1 1; EUPATORIUM PERFOLIATUM FLOWERING TOP 3 [hp_C]/1 1; GELSEMIUM SEMPERVIRENS ROOT 6 [hp_C]/1 1; STRYCHNOS NUX-VOMICA SEED 3 [hp_C]/1 1
INACTIVE INGREDIENTS: SUCROSE; LACTOSE, UNSPECIFIED FORM

ColdCalm Pellets

Active ingredients** (in each pellet)

Allium cepa 3C HPUS (0.05 mg)

Apis mellifica 6C HPUS (0.05 mg)

Belladonna 6C HPUS (0.05 mg)(contains less than 10^-15 mg atropine alkaloids)

Eupatorium perfoliatum 3C HPUS (0.05 mg)

Gelsemium sempervirens 6C HPUS (0.05 mg)

Kali bichromicum 6C HPUS (0.05 mg)

Nux vomica 3C HPUS (0.05 mg) (contains less than 10^-8 mg strychnine alkaloids)

Phytolacca decandra 6C HPUS (0.05 mg)

Pulsatilla 6C HPUS (0.05 mg)

The letters "HPUS" indicate that the components in this product are officially monographed in the Homeopathic Pharmacopoeia of the United States.

Purpose*

Relieves Cold Symptoms: Sneezing, Runny Nose, Occasional Minor Sore Throat, and Congestion

Uses*

temporarily relieves cold symptoms such as:

▪ sneezing ▪ runny nose ▪ nasal congestion ▪ occasional minor sore throat t

Do not use if you are allergic to Apis.

Ask a doctor before use if sore throat is severe, accompanied or followed by fever, headache, rash, nausea, or vomiting.

Stop use and ask a doctor if ▪ sore throat worsens or persists for more than 2 days ▪ nasal congestion worsens or lasts more than 5 days in children under 12 years of age or 7 days in adults ▪ new symptoms occur

PREGNANCY OR BREAST FEEDING

If pregnant or breast-feeding, ask a health professional before use.

Keep out of reach of children. In case of overdose, get medical help or contact a Poison Control Center right away.

Directions

- Adults and children 4 years of age and older: At the onset of symptoms, dissolve 5 pellets under the tongue every 15 minutes for 1 hour. Then, dissolve 5 pellets under the tongue every 6 hours. Decrease frequency with improvement.
- Children under 4 years of age: Ask a doctor.

Other information

- do not use if glued carton end flaps are open or if pellet dispenser seal is broken
- contains 0.25 g of sugar per dose

INACTIVE INGREDIENT

lactose, sucrose

Questions or comments?

1-800-264-7661

Made in France

Distributed by

Boiron Inc.

Newtown Square, PA

19073

2 PORTABLE TUBES

APPROX. 80 PELLETS EACH

TOTAL 160 PELLETS

Multi-Symptom Cold Relief*

No Known Drug Interactions

*CLAIMS BASED ON TRADITIONAL HOMEOPATHIC PRACTICE, NOT ACCEPTED MEDICAL EVIDENCE. NOT FDA EVALUATED.

**C,K,CK, and X are homeopathic dilutions: see BoironUSA.com/info for details.